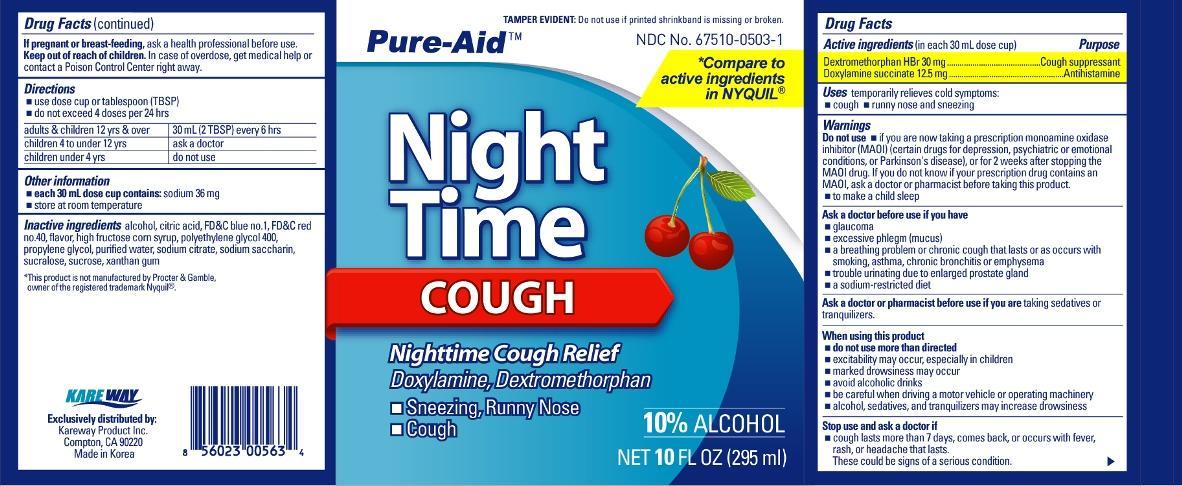 DRUG LABEL: Night Time Cough
NDC: 67510-0503 | Form: LIQUID
Manufacturer: Kareway Product, Inc.
Category: otc | Type: HUMAN OTC DRUG LABEL
Date: 20120711

ACTIVE INGREDIENTS: DEXTROMETHORPHAN HYDROBROMIDE 15 mg/15 mL; DOXYLAMINE SUCCINATE 6.25 mg/15 mL
INACTIVE INGREDIENTS: ALCOHOL; CITRIC ACID MONOHYDRATE; FD&C BLUE NO. 1; FD&C RED NO. 40; HIGH FRUCTOSE CORN SYRUP; POLYETHYLENE GLYCOLS; PROPYLENE GLYCOL; WATER; SACCHARIN SODIUM DIHYDRATE; SODIUM CITRATE; SUCROSE; SUCRALOSE; XANTHAN GUM

Drug Facts

Active ingredients (in each 30 ml dose cup)

Dextromethorphan HBr 30 mg

Doxylamine succinate 12.5 mg

Purpose

Cough suppressant

Antihistamine

Uses

temporarily relieves common cold symptoms:

- cough
- runny nose and sneezing

Warnings

Do not use

- if you are now taking a prescription monoamine oxidase inhibitor (MAOI) (certain drugs for depression, psychiatric, or emotional conditions, or Parkinson's disease), or for 2 weeks after stopping the MAOI drug. If you do not know if your prescription drug contains an MAOI, ask a doctor or pharmacist before taking this product.
- to make a child sleep

Ask a doctor before use if you have

- glaucoma
- excessive phlegm (mucus)
- a breathing problem or chronic cough that lasts or as occurs with smoking, asthma, chronic bronchitis or emphysema
- trouble urinating due to enlarged prostate gland
- a sodium-restricted diet

When using this product

- do not use more than directed
- excitability may occur, especially in children.
- marked drowsiness may occur
- avoid alcoholic drinks
- be careful when driving a motor vehicle or operating machinery
- alcohol, sedatives, and tranquilizers may increase drowsiness.

Stop use and ask a doctor if

- cough lasts more than 7 days, comes back, or is accompanied by fever, rash, or persistent headache. These could be signs of a serious condition.

If pregnant or breast-feeding,

ask a health professional before use.

Keep out of reach of children.

In case of overdose, get medical help or contact a Poison Control Center right away.

Directions

- use dose cup or tablespoon (TBSP)
- do not exceed 4 doses per 24 hours

adults and children 12 years and over | 2 TBSP (30ml) every 6 hours
children under 12 years | ask a doctor

Other information

- each 30mL dose cup contains: sodium 36 mg
- store at room temperature

Inactive ingredients

alcohol, citric acid, FD and C blue no.1, FD and C red no.40, flavor, high fructose corn syrup, polyethylene glycol, propylene glycol, purified water, saccharin sodium, sodium citrate, sucrose, sucralose, xanthan gum

Package label

Night Time Cough Relief